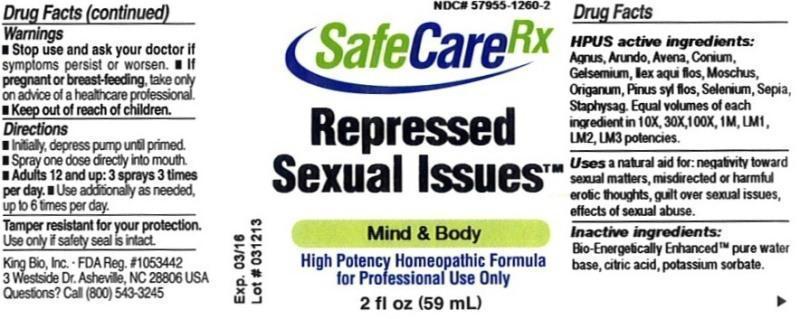 DRUG LABEL: Repressed Sexual Issues
NDC: 57955-1260 | Form: LIQUID
Manufacturer: King Bio Inc.
Category: homeopathic | Type: HUMAN PRESCRIPTION DRUG LABEL
Date: 20130417

ACTIVE INGREDIENTS: CHASTE TREE 10 [hp_X]/59 mL; ARUNDO PLINIANA ROOT 10 [hp_X]/59 mL; AVENA SATIVA FLOWERING TOP 10 [hp_X]/59 mL; CONIUM MACULATUM FLOWERING TOP 10 [hp_X]/59 mL; GELSEMIUM SEMPERVIRENS ROOT 10 [hp_X]/59 mL; ILEX AQUIFOLIUM FLOWERING TOP 10 [hp_X]/59 mL; MOSCHUS MOSCHIFERUS MUSK SAC RESIN 10 [hp_X]/59 mL; ORIGANUM MAJORANA WHOLE 10 [hp_X]/59 mL; PINUS SYLVESTRIS FLOWERING TOP 10 [hp_X]/59 mL; SELENIUM 10 [hp_X]/59 mL; SEPIA OFFICINALIS JUICE 10 [hp_X]/59 mL; DELPHINIUM STAPHISAGRIA SEED 10 [hp_X]/59 mL
INACTIVE INGREDIENTS: WATER; CITRIC ACID MONOHYDRATE; POTASSIUM SORBATE

Repressed Sexual Issues

Warnings

- Stop use and ask your doctor if symptoms persist or worsen.
- If pregnant or breast-feeding, take only on advice of a healthcare professional.
- Keep out of reach of children.

Tamper resistant for your protection. Use only if safety seal is intact.

Keep out of reach of children.

Directions

- Initially, depress pump until primed.
- Spray one dose directly into mouth.
- Adults 12 and up: 3 sprays 3 times per day.
- Use additionally as needed, up to 6 times per day.

HPUS Active Ingredients

Agnus castus, Arundo mauritanica, Avena sativa, Conium maculatum, Gelsemium sempervirens, Ilex aquifolium, flos, Moschus, Origanum majorana, Pinus sylvestris, flos, Selenium metallicum, Sepia, Staphysagria. Equal volumes of each ingredient in 10X, 30X, 100X, 1M, LM1, LM2 and LM3 potencies.

Indications and Usage

Uses a natural aid for: negativity toward sexual matters, misdirected or harmful erotic thoughts, guilt over sexual issues, effects of sexual abuse.

Inactive Ingredient

Bio-Energetically Enhanced™ pure water base, citric acid, potassium sorbate.

Purpose

Uses a natural aid for:

- negativity toward sexual matters
- misdirected or harmful erotic thoughts
- guilt over sexual issues
- effects of sexual abuse